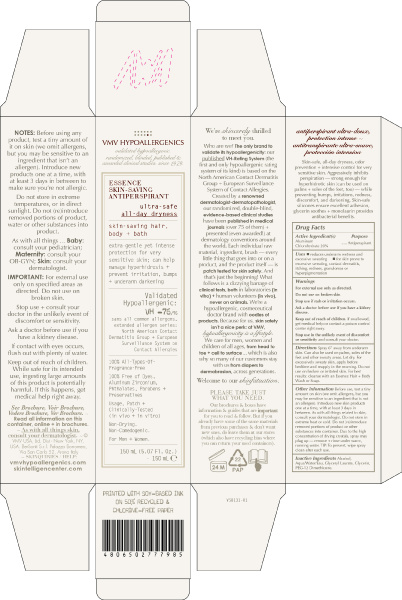 DRUG LABEL: ESSENCE SKIN-SAVING ANTIPERSPIRANT
NDC: 69774-751 | Form: SPRAY
Manufacturer: SKIN SCIENCES LABORATORY INC.
Category: otc | Type: HUMAN OTC DRUG LABEL
Date: 20170401

ACTIVE INGREDIENTS: ALUMINUM CHLOROHYDRATE 30 g/150 mL
INACTIVE INGREDIENTS: GLYCERYL LAURATE; GLYCERIN; DIMETHICONE; WATER

Active ingredient(s)

Aluminum Chlorohydrate 20%

Uses

- reduces underarm wetness and excessive sweating
- for skin prone to excessive sweating, contact dermatitis, itching, redness, granulomas or hyperpigmentation

Warnings

For external use only as directed.

Do not use on broken skin.

Stop use if rash or irritation occurs.

Ask a doctor before use if you have a kidney disease

Keep out of reach of children. If swallowed, get medical help or contact a poison control center right away.

Stop use in the unlikely event of discomfort or sensitivity and consult your doctor.

Directions

Spray 6” away from underarm skin. Can also be used on palms, soles of the feet and other sweaty areas. Let dry. For excessively sweaty skin, apply before bedtime and reapply in the morning. Do not use on broken or irritated skin. For best results: cleanse with an Essence Hair + Body Wash or Soap.

Other Information

Before use, test a tiny amount on skin (we omit allergens, but you may be sensitive to an ingredient that is not an allergen). Introduce new skin products one at a time, with at least 3 days in between. As with all things related to skin, consult your dermatologist. Do not store in extreme heat or cold. Do not (re)introduce removed portions of product or other substances into container. Due to the high concentration of drying crystals, spray may plug up – remove + rinse under warm, running water. TIP: To prevent, wipe spray clean after each use.

Inactive Ingredients

Alcohol, Aqua/Water/Eau, Glyceryl Laurate, Glycerin, PEG-12 Dimethicone.

Keep out of reach of children, If swallowed, get medical help or contact a poison control center right away.

PURPOSE

protection for very

sensitive skin; can help

manage hyperhidrosis +

prevent irritation, bumps

+ underarm darkening

PACKAGE LABEL

PRINCIPAL PANEL DISPLAY

VMV HYPOALLERGENICS

validated hypoallergenic.

randomized, blinded, published & awarded clinical studies. since 1979.

ESSENCE

SKIN-SAVING

ANTIPERSPIRANT

ultra-safe

all-day dryness

skin-saving hair,

body + bath

extra-gentle yet intense

protection for very

sensitive skin; can help

manage hyperhidrosis +

prevent irritation, bumps

+ underarm darkening

Validated

Hypoallergenic:

VH -76/76

sans all common allergens,

extended allergen series:

North American Contact

Dermatitis Group + European

Surveillance System on

Contact Allergies

100% All-Types-Of-

Fragrance-Free

100% Free of Dyes,

Aluminum Zirconium,

Phthalates, Parabens +

Preservatives

Usage, Patch +

Clinically-Tested

(in vivo + in vitro)

Non-Drying.

Non-Comedogenic.

For Men + Women.